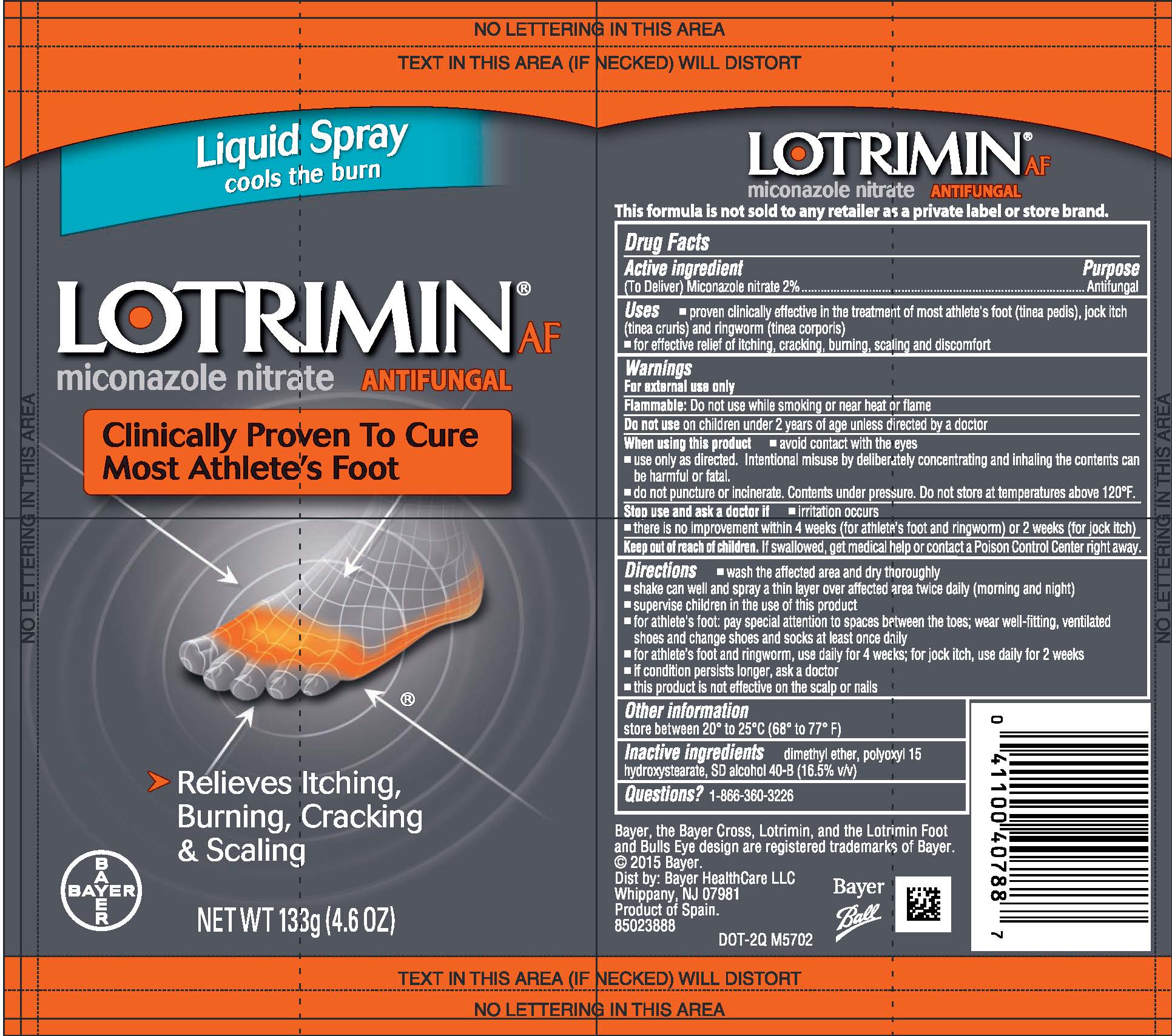 DRUG LABEL: Lotrimin AF
NDC: 11523-4327 | Form: SPRAY
Manufacturer: Bayer Healthcare LLC.
Category: otc | Type: HUMAN OTC DRUG LABEL
Date: 20241206

ACTIVE INGREDIENTS: MICONAZOLE NITRATE 20 mg/1 g
INACTIVE INGREDIENTS: DIMETHYL ETHER

Lotrimin® AF
Antifungal Liquid

Drug Facts

Active ingredient

(To Deliver) Miconazole nitrate 2%

Purpose

Antifungal

Uses

- proven clinically effective in the treatment of most athlete's foot (tinea pedis), jock itch (tinea cruris) and ringworm (tinea corporis)
- for effective relief of itching, cracking, burning, scaling and discomfort

Warnings

For external use only

Flammable

Do not use while smoking or near heat or flame

Do not use on children under 2 years of age unless directed by a doctor

When using this product

- avoid contact with the eyes
- use only as directed. Intentional misuse by deliberately concentrating and inhaling the contents can be harmful or fatal
- Do not puncture or incinerate. Contents under pressure. Do not store at temperatures above 120°F.

Stop use and ask a doctor if

- irritation occurs
- there is no improvement within 4 weeks (for athlete's foot and ringworm) or 2 weeks (for jock itch)

Keep out of reach of children. If swallowed, get medical help or contact a Poison Control Center right away.

Directions

- wash affected area and dry thoroughly
- shake can well and spray a thin layer over affected area twice daily (morning and night)
- supervise children in the use of this product
- for athlete's foot: pay special attention to spaces between the toes; wear well-fitting, ventilated shoes and change shoes and socks at least once daily
- for athlete's foot and ringworm, use daily for 4 weeks; for jock itch, use daily for 2 weeks
- if condition persists longer, ask a doctor
- this product is not effective on the scalp or nails

Other information

store between 20° to 25°C (68° to 77°F)

Inactive ingredients

dimethyl ether, polyoxyl 15 hydroxystearate, sd alcohol 40-B (16.5% v/v)

Questions?

1-866-360-3266

Distribution

Distributed by Bayer HealthCare LLC

Whippany, NJ 07981 USA

PRINCIPAL DISPLAY PANEL - 133 g Can Label

Liquid Spray
cools the burn

NDC 11523-4327-01

LOTRIMIN® AF
ANTIFUNGAL
miconazole nitrate

Clinically Proven To Cure
Most Athlete's Foot

- Relieves Itching,
  Burning, Cracking
  & Scaling

NET WT 133g (4.6 OZ)